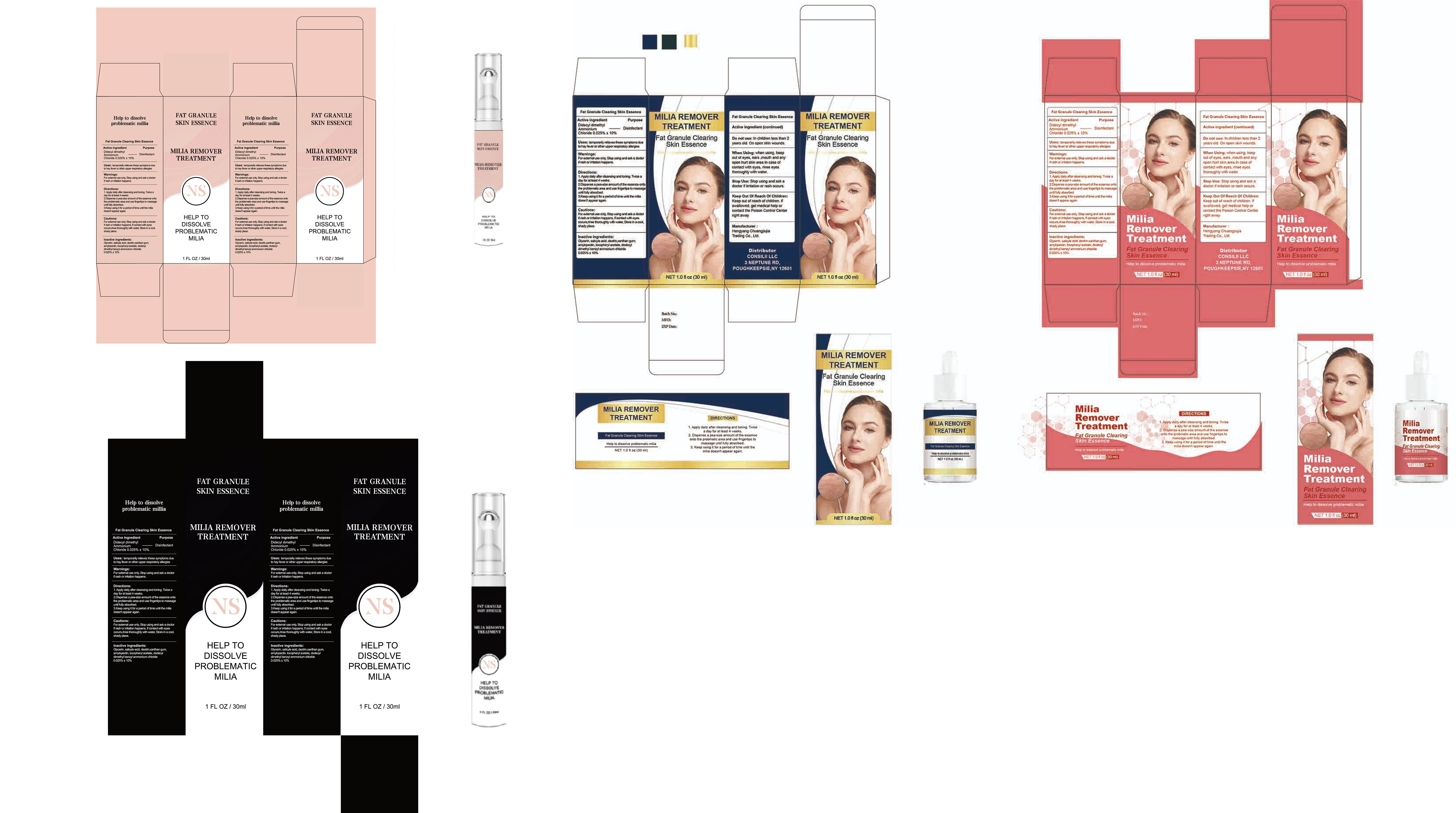 DRUG LABEL: MILIA REMOVER TREATMENT
NDC: 84735-006 | Form: LIQUID
Manufacturer: Hengyang Chuangjiujia Trading Co., Ltd.
Category: otc | Type: HUMAN OTC DRUG LABEL
Date: 20250521

ACTIVE INGREDIENTS: DIDECYLDIMONIUM 0.025 g/100 mL
INACTIVE INGREDIENTS: GLYCERIN; XANTHAN GUM; .ALPHA.-TOCOPHEROL ACETATE; SALICYLIC ACID; DIHYDROMYRICETIN

MILIA REMOVER TREATMENT

ACTIVE INGREDIENT

Dideoyl Dimethyl Ammonium Chloride 0.025%

PURPOSE

Disinfectant

INDICATIONS AND USAGE

Uses: temporarily relieves these symptoms dueto hay fever or other upper respiratory allergies

WARNINGS

For extemal use only, Stop using and ask a doctorif rash or initation happens.

Do not use: In children less than 2years old. On open skin wounds.

WHEN USING

When Using: when using, keepout of eyes, ears ,mouth and anyopen hurt skin area.In case ofcontact with eyes, rinse eyesthoroughly with water.

Stop Use: Stop using and ask adoctor if irritation or rash occurs

Keep out of reach of children. lf swallowed, get medical help orcontact the Poison Control Centerright away.

DOSAGE AND ADMINISTRATION

1. Apply daily after cleansing and toning. Twice aday for at least 4 weeks.
2.Dispense a pea-size amount of the essence ontothe problematic area and use fingertips to massageuntil fully absorbed.
3.keep using it for a period of time until the miliadoesn't appear again.

INACTIVE INGREDIENT

Glycerin
Salicylic acid
Xanthan gum
Ampelopsin
Tocopheryl Acetate